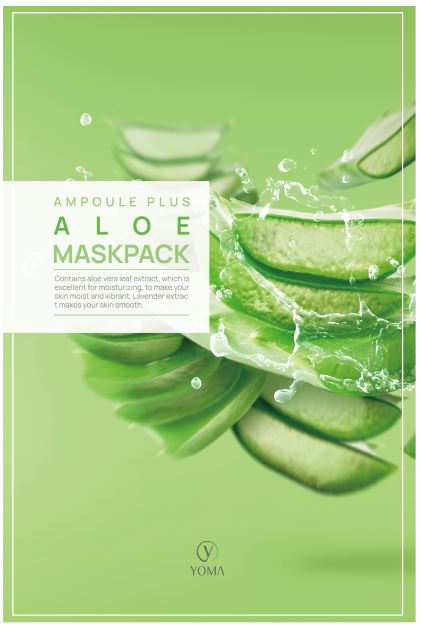 DRUG LABEL: YOMA AMPOULE PLUS ALOE MASK PACK
NDC: 82083-0007 | Form: LIQUID
Manufacturer: LAON COMMERCE co ltd
Category: otc | Type: HUMAN OTC DRUG LABEL
Date: 20211228

ACTIVE INGREDIENTS: ADENOSINE 0.04 g/100 g
INACTIVE INGREDIENTS: WATER

YOMA AMPOULE PLUS ALOE MASK PACK

ACTIVE INGREDIENT

Adenosine

INACTIVE INGREDIENT

Water, Dipropylene Glycol, Glycerin, Butylene Glycol, 1,2-Hexanediol, Polysorbate 80, Carbomer, Triethanolamine, Lavandula Angustifolia (Lavender) Extract, Portulaca Oleracea Extract, Nelumbo Nucifera Flower Extract, Olea Europaea (Olive) Fruit Extract, Melaleuca Alternifolia (Tea Tree) Extract, Tremella Fuciformis (Mushroom) Extract, Rosmarinus Officinalis (Rosemary) Leaf Extract, Chamomilla Recutita (Matricaria) Flower Extract, Centella Asiatica Extract, Salvia Officinalis (Sage) Leaf Extract, Salix Alba (Willow) Bark Extract, Aloe Barbadensis Leaf Extract, Sodium Hyaluronate, Allantoin, Xanthan Gum, Methylparaben, Disodium EDTA, Betaine, Fragrance, Ethylhexylglycerin

PURPOSE

It helps to improve wrinkles on the skin.

KEEP OUT OF REACH OF THE CHILDREN

INDICATIONS AND USAGE

After facial wash, use a toner, Put the mask sheet on your face and take it off after 10~20 minutes.

WARNINGS

1. When using cosmetics or after use, consult with a specialist it there is any abnormal symptom or side effect such as red spot, swelling, or itching, etc.
2. Do not use in wounded areas.
3. Precautions for storage and handling
  A) Keep out of reach of children
  B) Keep away from direct sunlight.
4. Avoid the eyes.
5. Use immediately after opening

DOSAGE AND ADMINISTRATION

external use only